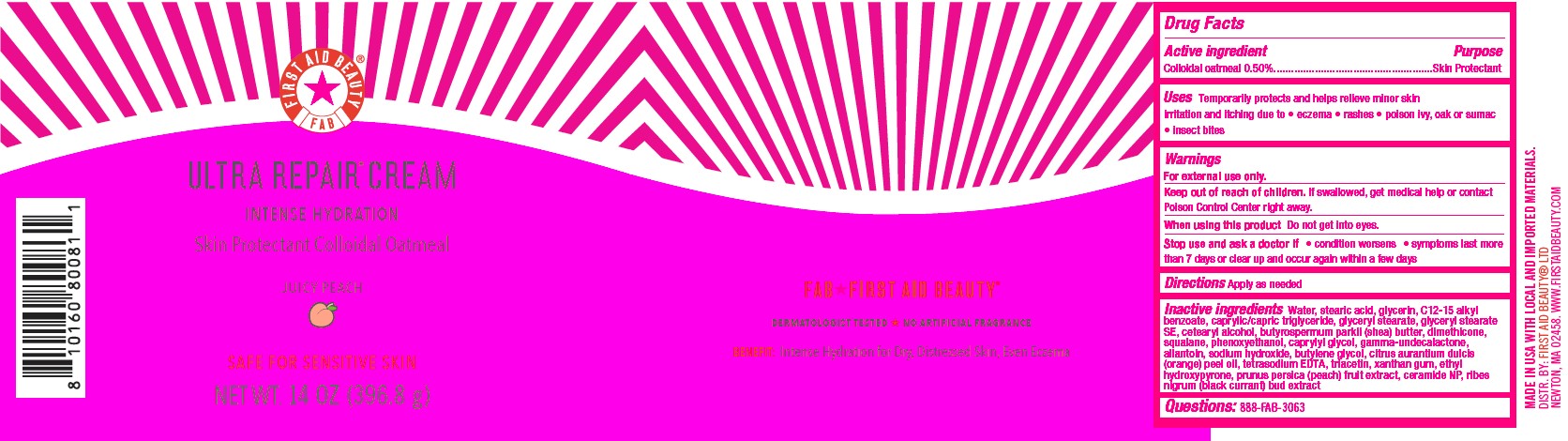 DRUG LABEL: First Aid Beauty FAB Ultra Repair Cream Intense Hydration Skin Protectant Juicy Peach
NDC: 84126-104 | Form: CREAM
Manufacturer: The Procter & Gamble Manufacturing Company
Category: otc | Type: HUMAN OTC DRUG LABEL
Date: 20250319

ACTIVE INGREDIENTS: OATMEAL 0.5 g/100 g
INACTIVE INGREDIENTS: TRIACETIN; ETHYL HYDROXYPYRONE; GLYCERYL STEARATE SE; CETEARYL ALCOHOL; SQUALANE; DIMETHICONE; TETRASODIUM EDTA; C12-15 ALKYL BENZOATE; CAPRYLYL GLYCOL; SODIUM HYDROXIDE; PHENOXYETHANOL; BUTYROSPERMUM PARKII (SHEA) BUTTER; WATER; GLYCERIN; ALLANTOIN; GLYCERYL STEARATE; CAPRYLIC/CAPRIC TRIGLYCERIDE; XANTHAN GUM; CERAMIDE NP; CITRUS AURANTIUM DULCIS (ORANGE) PEEL OIL; PRUNUS PERSICA (PEACH) FRUIT; BUTYLENE GLYCOL; GAMMA-UNDECALACTONE; STEARIC ACID; RIBES NIGRUM FLOWER BUD

First Aid Beauty FAB Ultra Repair Cream Intense Hydration Skin Protectant Juicy Peach

Drug Facts

Active ingredients

Colloidal Oatmeal 0.5%

Purpose

Skin Protectant

Uses

- Temporarily protects and helps relieve minor skin irritation and itching due to eczema, rashes, poison ivy, oak or sumac, insect bites

Warnings

For external use only.

Keep out of reach of children. If swallowed, get medical help or contact a Poison Control Center right away.

WHEN USING

Do not get into eyes.

Stop use and ask a doctor if condition worsens, symptoms last more than 7 days or clear up and occur again within a few days

Directions

Apply as needed

INACTIVE INGREDIENT

Water, stearic acid, glycerin, C12-15 alkyl benzoate, caprylic/capric triglyceride, glyceryl stearate, glyceryl stearate SE, cetearyl alcohol, butyrospermum parkii (shea) butter, dimethicone, squalane, phenoxyethanol, caprylyl glycol, gamma-undecalactone, allantoin, sodium hydroxide, butylene glycol, citrus aurantium dulcis (orange) peel oil, tetrasodium EDTA, triacetin, xanthan gum, ethyl hydroxypyrone, prunus persica (peach) fruit extract, ceramide NP, ribes nigrum (black currant) bud extract

Questions:

888-FAB-3063

MADE IN USA

FIRST AID BEAUTY LTD

NEWTON, MA 02458

WWW.FIRSTAIDBEAUTY.COM

PRINCIPAL DISPLAY PANEL - 396.8 g (14 oz)

First Aid Beauty

FAB

Ultra Repair® Cream

Intense Hydration

Skin Protectant Colloidal Oatmeal

JUICY PEACH

Net Wt. 396.8 g (14 oz)